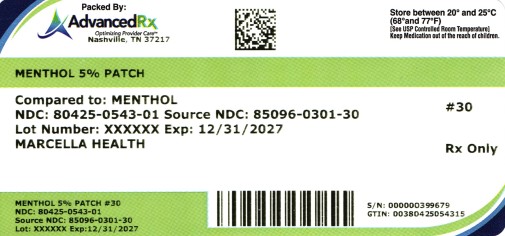 DRUG LABEL: MENTHOL 5%
NDC: 80425-0543 | Form: PATCH
Manufacturer: Advanced Rx of Tennessee, LLC
Category: otc | Type: HUMAN OTC DRUG LABEL
Date: 20250808

ACTIVE INGREDIENTS: MENTHOL, (+)- 500 mg/10 g
INACTIVE INGREDIENTS: ARNICA MONTANA FLOWER; CAMELLIA SINENSIS LEAF; POVIDONE K90; PETROLATUM; HYDROXYACETOPHENONE; TITANIUM DIOXIDE; PROPYLENE GLYCOL; GLYCERIN; KAOLIN; TARTARIC ACID; SODIUM POLYACRYLATE (2500000 MW); DIHYDROXYALUMINUM AMINOACETATE ANHYDROUS; METHYLPARABEN; EDETATE DISODIUM; POLYSORBATE 80; PROPYLPARABEN; WATER; CELLULOSE GUM; FRANKINCENSE; MINERAL OIL; ALOE VERA LEAF

Menthol Patch
Menthol 5% | Pain Relieving Patch

ACTIVE INGREDIENTS (IN EACH PATCH)

Menthol 5%

USES

Temporary relief from minor aches and pains of sore muscles and joints

associated with:

- arthrits
- backache
- strains
- sprains

PURPOSE

External Analgesic

WARNINGS

For external use only.

CONSULT WITH A DOCTOR OR PHARMACIST BEFORE CONTINUED USE IF YOU HAVE

Sensitive Skin

WHEN USING THIS PRODUCT

- Use only as directed
- Do not bandage tightly or use with heating pad or device
- Avoid contact with the eyes or mucous membranes
- Do not apply to wounds or damaged skin
- Do not use with other ointments,creams,sprays, or liniments
- Do not apply to irritated skin
- Store in a cool, dry place away from sunlight

STOP USE AND ASK A DOCTOR IF

Burning discomfort or excessive skin irritation develops, condition wrosens, or if symptoms persist for more than 7 days, or clear up and occur again within a few days

IF YOU ARE PREGNANT OR BREAST-FEEDING: Consult with physician before use of this product.

KEEP OUT OF THE REACH OF CHILDREN

If accidentally ingested, get medical help or contact a Poison Control Center immediately

DIRECTIONS:

Adults and Children 12 Years of Age or Over:Clean and dry the affected area, partially peel back the protective film and apply the exposed patch to the site of pain. Carefully remove the remaining film while pressing patch to skin and leave in place for up to 8 hours. Use on affected areas not more than 4 times daily. Wash hands with cool water after use.

Children Under 12 Years of Age:Consult physician.

OTHER INGREDIENTS

Aloe Barbadensis Leaf Extract, Arnica Montana Flower Extract, Boswellia Carterii Resin Extract, Camellia Sinensis Leaf Extract, Carboxymethylcellulose Sodium, Dihydroxyaluminum Aminoacetate, Edetate Disodium, Glycerin, Hydroxyacetophenone, Kaolin, Tartaric Acid, Mineral Oil, Petrolatum, Polyacrylic Acid, Polysorbate 80, Propylene Glycol, Sodium Polyacrylate, Titanium dioxide, Water

QUESTIONS?

Call toll-free: (307) 410-3813 or Email: info@marcellahealth.com